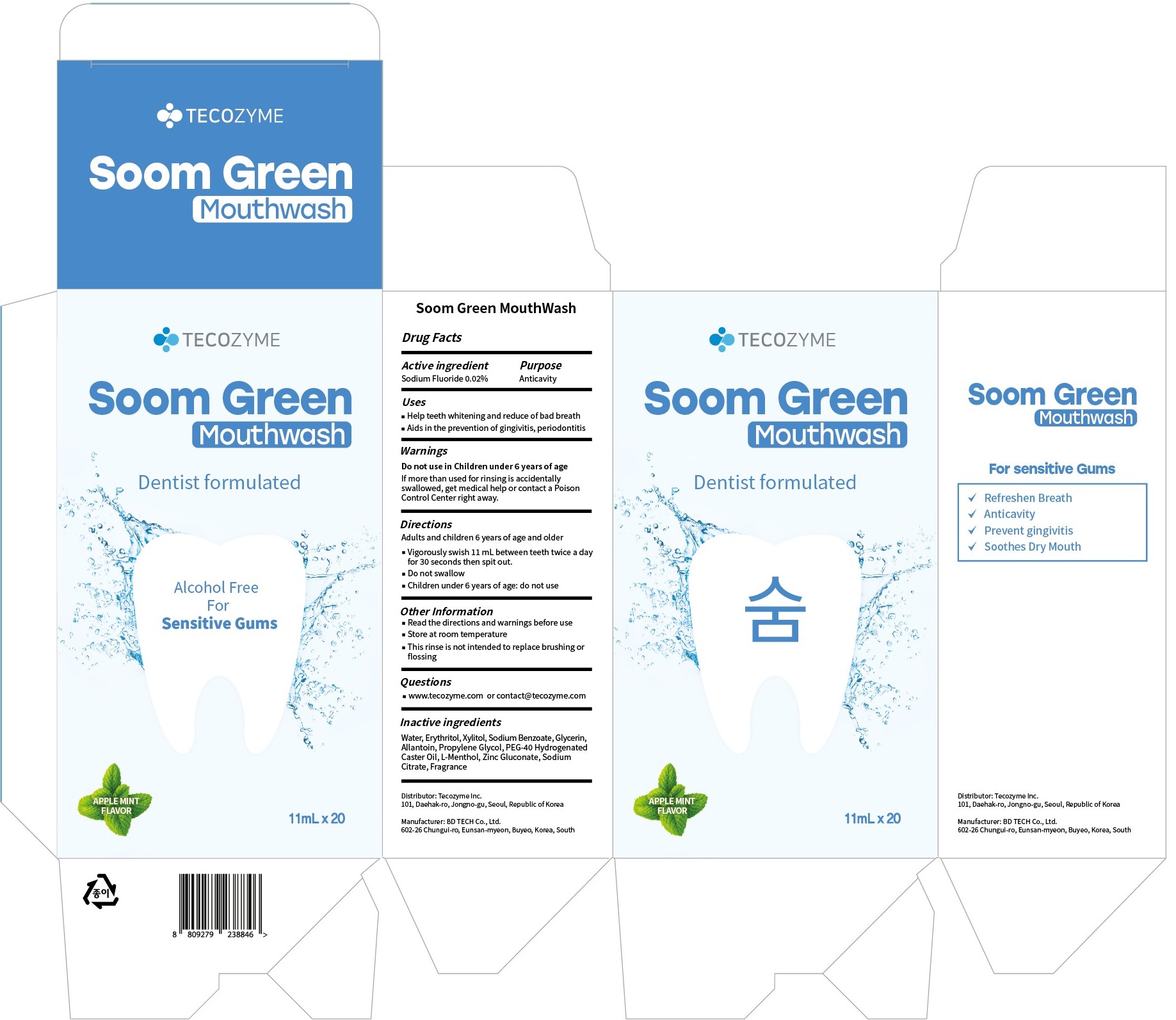 DRUG LABEL: Soom Green Mouthwash
NDC: 79717-0010 | Form: LIQUID
Manufacturer: TECOZYME INC
Category: otc | Type: HUMAN OTC DRUG LABEL
Date: 20210817

ACTIVE INGREDIENTS: SODIUM FLUORIDE 0.02 g/100 mL
INACTIVE INGREDIENTS: Water; Erythritol; Xylitol

ACTIVE INGREDIENT

Sodium Fluoride 0.02%

PURPOSE

Anticavity

Uses

■ Help teeth whitening and reduce of bad breath
■ Aids in the prevention of gingivitis, periodontitis

WARNINGS

Do not use in Children under 6 years of age
If more than used for rinsing is accidentally swallowed, get medical help or contact a Poison Control Center right away.

KEEP OUT OF REACH OF CHILDREN

Do not use in Children under 6 years of age
If more than used for rinsing is accidentally swallowed, get medical help or contact a Poison Control Center right away.

Directions

Adults and children 6 years of age and older
■ Vigorously swish 11 mL between teeth twice a day for 30 seconds then spit out.
■ Do not swallow
■ Children under 6 years of age: do not use

Other Information

■ Read the directions and warnings before use
■ Store at room temperature
■ This rinse is not intended to replace brushing or flossing

QUESTIONS

■ www.tecozyme.com or contact@tecozyme.com

INACTIVE INGREDIENTS

Water, Erythritol, Xylitol, Sodium Benzoate, Glycerin, Allantoin, Propylene Glycol, PEG-40 Hydrogenated Caster Oil, L-Menthol, Zinc Gluconate, Sodium Citrate, Fragrance